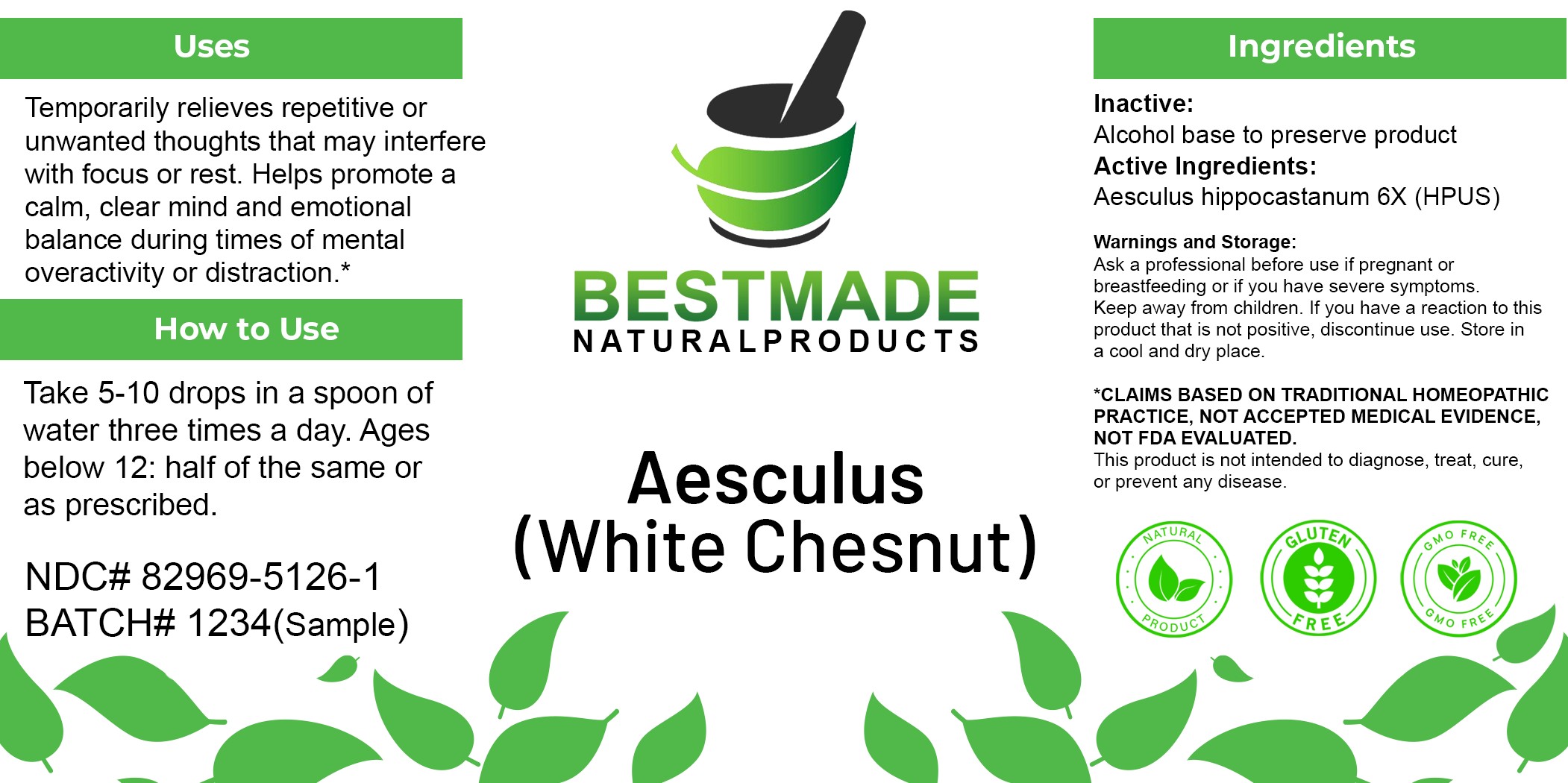 DRUG LABEL: Aesculus (White Chestnut)
NDC: 82969-5126 | Form: LIQUID
Manufacturer: Bestmade Natural Products
Category: homeopathic | Type: HUMAN OTC DRUG LABEL
Date: 20250609

ACTIVE INGREDIENTS: HORSE CHESTNUT 6 [hp_X]/1 mL
INACTIVE INGREDIENTS: ALCOHOL 0.985 mL/1 mL

White Chestnut

INACTIVE INGREDIENT

Alcohol base to preserve product

DOSAGE AND ADMINISTRATION

Dosage Instructions: Take 5-10 drops in a spoon of water three times a day. Ages below 12: half of the same or as prescribed.

Active Ingredient: Aesculus hippocastanum 6X (HPUS).

KEEP OUT OF REACH OF CHILDREN

Warnings and Storage:

Ask a professional before use if pregnant or breastfeeding or if you have severe symptoms. Keep away from children. If you have a reaction to this product that is not positive, discontinue use. Store in a cool and dry place.

*CLAIMS BASED ON TRADITIONAL HOMEOPATHIC PRACTICE, NOT ACCEPTED MEDICAL EVIDENCE, NOT FDA EVALUATED. This product is not intended to diagnose, treat, cure, or prevent any disease.

Warnings and Storage:

Ask a professional before use if pregnant or breastfeeding or if you have severe symptoms. Keep away from children. If you have a reaction to this product that is not positive, discontinue use. Store in a cool and dry place.

*CLAIMS BASED ON TRADITIONAL HOMEOPATHIC PRACTICE, NOT ACCEPTED MEDICAL EVIDENCE, NOT FDA EVALUATED. This product is not intended to diagnose, treat, cure, or prevent any disease.

INDICATIONS AND USAGE

Use: Temporarily relieves repetitive or unwanted thoughts that may interfere with focus or rest. Helps promote a calm, clear mind and emotional balance during times of mental overactivity or distraction.*

PURPOSE

Use: Temporarily relieves repetitive or unwanted thoughts that may interfere with focus or rest. Helps promote a calm, clear mind and emotional balance during times of mental overactivity or distraction.*

Entire Package Label